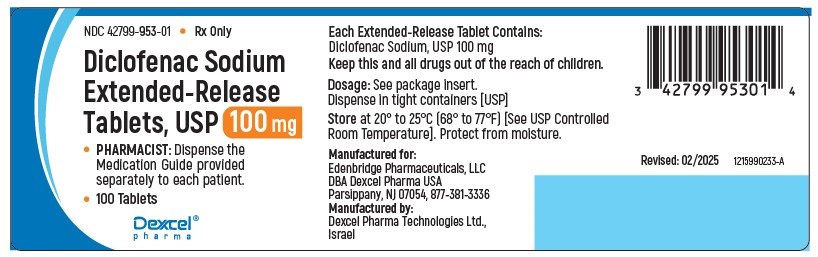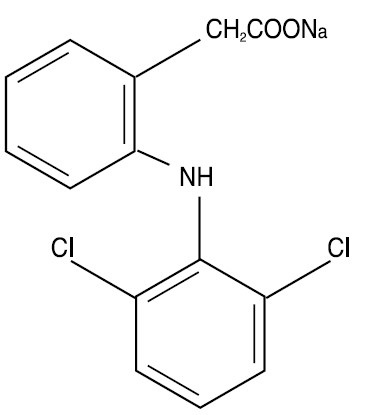 DRUG LABEL: Diclofenac Sodium
NDC: 42799-953 | Form: TABLET, EXTENDED RELEASE
Manufacturer: Edenbridge Pharmaceuticals LLC.
Category: prescription | Type: Human Prescription Drug Label
Date: 20260225

ACTIVE INGREDIENTS: DICLOFENAC SODIUM 100 mg/1 1
INACTIVE INGREDIENTS: CARNAUBA WAX; CETOSTEARYL ALCOHOL; SILICON DIOXIDE; ACACIA; MAGNESIUM STEARATE; SUCROSE; TALC; TITANIUM DIOXIDE; POLYETHYLENE GLYCOL 400; POVIDONE K30; HYPROMELLOSE 2910 (5 MPA.S); FERRIC OXIDE RED; COPOVIDONE K25-31

Diclofenac Sodium Extended-Release Tablets, USP, Tablets of 100 mg
Prescribing Information
Rx only

WARNING: RISK OF SERIOUS CARDIOVASCULAR AND GASTROINTESTINAL EVENTS

Cardiovascular Thrombotic Events
• Nonsteroidal anti-inflammatory drugs (NSAIDs) cause an increased risk of serious cardiovascular thrombotic events, including myocardial infarction and stroke, which can be fatal. This risk may occur early in treatment and may increase with duration of use (see WARNINGS).
• Diclofenac Sodium extended-release tablets, USP are contraindicated in the setting of coronary artery bypass graft (CABG) surgery (see CONTRAINDICATIONS, WARNINGS).
Gastrointestinal Bleeding, Ulceration, and Perforation
• NSAIDs cause an increased risk of serious gastrointestinal (GI) adverse events, including bleeding, ulceration, and perforation of the stomach or intestines, which can be fatal. These events can occur at any time during use and without warning symptoms. Elderly patients and patients with a prior history of peptic ulcer disease and/or GI bleeding are at greater risk for serious GI events (see WARNINGS).

DESCRIPTION

Diclofenac sodium extended-release tablets, USP is a benzeneacetic acid derivative. Diclofenac sodium extended-release tablets of 100 mg (pink) are available for oral administration. Diclofenac sodium is a white or slightly yellowish crystalline powder and is sparingly soluble in water at 25°C. The chemical name is 2-[(2,6-dichlorophenyl)amino] benzeneacetic acid, monosodium salt. The molecular weight is 318.14. Its molecular formula is C14H10Cl2NNaO2, and it has the following structural formula:

The inactive ingredients in diclofenac sodium extended-release tablets include: carnauba wax, cetostearyl alcohol, colloidal silicon dioxide, compressible sugar, copovidone, gum acacia, hydroxypropyl methylcellulose, iron oxide red, magnesium stearate, polyethylene glycol, povidone, sucrose, talc, titanium dioxide.

Meets USP Dissolution Test 2.

CLINICAL PHARMACOLOGY

Mechanism of Action

Diclofenac sodium extended-release tablets have analgesic, anti-inflammatory, and antipyretic properties.
The mechanism of action of diclofenac sodium extended-release tablets, like that of other NSAIDs, is not completely understood but involves inhibition of cyclooxygenase (COX-1 and COX-2).
Diclofenac is a potent inhibitor of prostaglandin synthesis in vitro. Diclofenac concentrations reached during therapy have produced in vivo effects. Prostaglandins sensitize afferent nerves and potentiate the action of bradykinin in inducing pain in animal models. Prostaglandins are mediators of inflammation. Because diclofenac is an inhibitor of prostaglandin synthesis, its mode of action may be due to a decrease of prostaglandins in peripheral tissues.

Pharmacokinetics

Absorption
Diclofenac is 100% absorbed after oral administration compared to intravenous (IV) administration as measured by urine recovery. However, due to firstpass metabolism, only about 50% of the absorbed dose is systemically available (see Table 1). When diclofenac sodium extended-release tablet are taken with food, there is a delay of 1 to 2 hours in the Tmax and a 2-fold increase in Cmax values. The extent of absorption of diclofenac, however, is not significantly affected by food intake.

Table 1. Pharmacokinetic Parameters for Diclofenac

PK Parameter | Normal Healthy Adults (18 to 48 years)
PK Parameter | Mean | Coefficient of Variation (%)
Absolute Bioavailability (%) [N=7] | 55 | 40
Tmax (hr) [N = 12] | 5.3 | 28
Oral clearance (CL/F; mL/ min) [N = 12] | 895 | 56
Renal clearance (% unchanged drug in urine) [N = 7] | <1 | -
Apparent volume of Distribution (V/F; L/kg) [N = 56] | 1.4 | 58
Terminal half-life (hr) [N = 56] | 2.3 | 4.8

Distribution

The apparent volume of distribution (V/F) of diclofenac sodium is 1.4 L/kg. Diclofenac is more than 99% bound to human serum proteins, primarily to albumin. Serum protein binding is constant over the concentration range (0.15 to 105 mcg/mL) achieved with recommended doses.
Diclofenac diffuses into and out of the synovial fluid. Diffusion into the joint occurs when plasma levels are higher than those in the synovial fluid, after which the process reverses and synovial fluid levels are higher than plasma levels. It is not known whether diffusion into the joint plays a role in the effectiveness of diclofenac.

Elimination

Metabolism
Five diclofenac metabolites have been identified in human plasma and urine. The metabolites include 4’-hydroxy-, 5-hydroxy-, 3’-hydroxy-, 4’, 5-dihydroxy- and 3’-hydroxy-4’-methoxy-diclofenac. The major diclofenac metabolite, 4'-hydroxy-diclofenac, has very weak pharmacologic activity. The formation of 4'-hydroxy diclofenac is primarily mediated by CYP2C9. Both diclofenac and its oxidativemetabolites undergo glucuronidation or sulfation followed by biliary excretion. Acyl glucuronidation mediated by UGT2B7 and oxidation mediated by CYP2C8 may also play a role in diclofenac metabolism. CYP3A4 is responsible for the formation of minor metabolites, 5-hydroxy- and 3’-hydroxy-diclofenac. In patients with renal dysfunction, peak concentrations of metabolites 4’-hydroxy- and 5-hydroxydiclofenac were approximately 50% and 4% of the parent compound after single oral dosing compared to 27% and 1% in normal healthy subjects.
Excretion
Diclofenac is eliminated through metabolism and subsequent urinary and biliary excretion of the glucuronide and the sulfate conjugates of the metabolites. Little or no free unchanged diclofenac is excreted in the urine. Approximately 65% of the dose is excreted in the urine and approximately 35% in the bile as conjugates of unchanged diclofenac plus metabolites. Because renal elimination is not a significant pathway of elimination for unchanged diclofenac, dosing adjustment in patients with mild to moderate renal dysfunction is not necessary. The terminal half-life of unchanged diclofenac is approximately 2 hours.

Special Populations

Pediatric:The pharmacokinetics of diclofenac sodium extended- release tablets has not been investigated in pediatric patients.
Race: Pharmacokinetic differences due to race have not been identified.
Hepatic Impairment: Hepatic metabolism accounts for almost 100% of diclofenac sodium extended-release tablets elimination, so patients with hepatic disease may require reduced doses of diclofenac sodium extended-release tablets compared to patients with normal hepatic function.
Renal Impairment: Diclofenac pharmacokinetics has been investigated in subjects with renal insufficiency. No differences in the pharmacokinetics of diclofenac have been detected in studies of patients with renal impairment. In patients with renal impairment (inulin clearance 60 to 90, 30 to 60, and less than 30 mL/min; N=6 in each group), area under the curve (AUC) values and elimination rate were comparable to those in healthy subjects.

Drug Interaction Studies

Voriconazole: When co-administered with voriconazole (inhibitor of CYP2C9, 2C19 and 3A4 enzyme), the Cmax and AUC of diclofenac increased by 114% and 78%, respectively (see PRECAUTIONS; Drug Interactions).
Aspirin: When NSAIDs were administered with aspirin, the protein binding of NSAIDs were reduced, although the clearance of free NSAID was not altered. The clinical significance of this interaction is not known. See Table 2 for clinically significant drug interactions of NSAIDs with aspirin (see PRECAUTIONS; Drug Interactions).

INDICATIONS & USAGE

Carefully consider the potential benefits and risks of diclofenac sodium extended release tablets, USP and other treatment options before deciding to use diclofenac sodium extended-release tablets. Use the lowest effective dose for the shortest duration consistent with individual patient treatment goals (see WARNINGS; Gastrointestinal Bleeding, Ulceration, and Perforation).
Diclofenac sodium extended-release tablets are indicated:
• for relief of the signs and symptoms of osteoarthritis
• for relief of the signs and symptoms of rheumatoid arthritis

CONTRAINDICATIONS

Diclofenac sodium extended-release tablets, USP are contraindicated in the following patients:
• Known hypersensitivity (e.g., anaphylactic reactions and serious skin reactions) to diclofenac or any components of the drug product (see WARNINGS; Anaphylactic Reactions, Serious Skin Reactions).
• History of asthma, urticaria, or allergic-type reactions after taking aspirin or other NSAIDs. Severe, sometimes fatal, anaphylactice reactions to NSAIDs have been reported in such patients (see WARNINGS; Anaphylactic Reactions, PRECAUTIONS; Exacerbation of Asthma Related to Aspirin Sensitivity).
• In the setting of coronary artery bypass graft (CABG) surgery (see WARNINGS; Cardiovascular Thrombotic Events).

WARNINGS

Cardiovascular Thrombotic Events
Clinical trials of several COX-2 selective and nonselective NSAIDs of up to 3 years duration have shown an increased risk of serious cardiovascular (CV) thrombotic events, including myocardial infarction (MI) and stroke, which can be fatal. Based on available data, it is unclear that the risk for CV thrombotic events is similar for all NSAIDs. The relative increase in serious CV thrombotic events over baseline conferred by NSAID use appears to be similar in those with and without known CV disease or risk factors for CV disease. However, patients with known CV disease or risk factors had a higher absolute incidence of excess serious CV thrombotic events, due to their increased baseline rate. Some observational studies found that this increased risk of serious CV thrombotic events began as early as the first weeks of treatment. The increase in CV thrombotic risk has been observed most consistently at higher doses.
To minimize the potential risk for an adverse CV event in NSAID-treated patients, use the lowest effective dose for the shortest duration possible. Physicians and patients should remain alert for the development of such events, throughout the entire treatment course, even in the absence of previous CV symptoms. Patients should be informed about the symptoms of serious CV events and the steps to take if they occur.
There is no consistent evidence that concurrent use of aspirin mitigates the increased risk of serious CV thrombotic events associated with NSAID use. The concurrent use of aspirin and an NSAID, such as diclofenac, increases the risk of serious gastrointestinal (GI) events (see WARNINGS; Gastrointestinal Bleeding, Ulceration, and Perforation).
Status Post Coronary Artery Bypass Graft (CABG) Surgery
Two large, controlled, clinical trials of a COX-2 selective NSAID for the treatment of pain in the first 10 to 14 days following CABG surgery found an increased incidence of myocardial infarction and stroke. NSAIDs are contraindicated in the setting of CABG (see CONTRAINDICATIONS).
Post-MI Patients
Observational studies conducted in the Danish National Registry have demonstrated that patients treated with NSAIDs in the post-MI period were at increased risk of reinfarction, CV-related death, and all-cause mortality beginning in the first week of treatment. In this same cohort, the incidence of death in the first year post-MI was 20 per 100 person years in NSAID-treated patients compared to 12 per 100 person years in non-NSAID exposed patients. Although the absolute rate of death declined somewhat after the first year post-MI, the increased relative risk of death in NSAID users persisted over at least the next four years of follow-up.
Avoid the use of diclofenac sodium extended-release tablets in patients with a recent MI unless the benefits are expected to outweigh the risk of recurrent CV thrombotic events. If diclofenac sodium extended-release tablets are used in patients with a recent MI, monitor patients for signs of cardiac ischemia.

Gastrointestinal Bleeding, Ulceration, and Perforation

NSAIDs, including diclofenac, can cause serious gastrointestinal (GI) adverse events, including inflammation, bleeding, ulceration, and perforation of the esophagus, stomach, small intestine, or large intestine, which can be fatal. These serious adverse events can occur at any time, with or without warning symptoms, in patients treated with NSAIDs. Only one in five patients, who develop a serious upper GI adverse event on NSAID therapy, is symptomatic. Upper GI ulcers, gross bleeding, or perforation caused by NSAIDs occurred in approximately 1% of patients treated for 3 to 6 months, and in about 2% to 4% of patients treated for one year. However, even short-term therapy is not without risk.
Risk Factors for GI Bleeding, Ulceration, and Perforation
Patients with a prior history of peptic ulcer disease and/or GI bleeding who use NSAIDs had a greater than 10-fold increased risk for developing a GI bleed compared to patients without these risk factors. Other factors that increase the risk of GI bleeding in patients treated with NSAIDs include longer duration of NSAID therapy, concomitant use of oral corticosteroids, aspirin, anticoagulants, or selective serotonin reuptake inhibitors (SSRIs); smoking, use of alcohol, older age, and poor general health status. Most postmarketing reports of fatal GI events occurred in elderly or debilitated patients. Additionally, patients with advanced liver disease and/or coagulopathy are at increased risk for GI bleeding.
Strategies to Minimize the GI Risks in NSAID-treated patients:
• Use the lowest effective dose for the shortest possible duration.
• Avoid administration of more than one NSAID at a time
• Avoid use in patients at higher risk unless benefits are expected to outweigh the increased risk of bleeding. For such patients, as well as those with active GI bleeding, consider alternate therapies other than NSAIDs.
• Remain alert for signs and symptoms of GI ulceration and bleeding during NSAID therapy.
• If a serious GI adverse event is suspected, promptly initiate evaluation and treatment, and discontinue diclofenac sodium extended-release tablets until a serious GI adverse event is ruled out.
• In the setting of concomitant use of low-dose aspirin for cardiac prophylaxis, monitor patients more closely for evidence of GI bleeding (see PRECAUTIONS; Drug Interactions).
Hepatotoxicity
In clinical trials of diclofenac-containing products, meaningful elevations (i.e., more than 3 times the upper limit of normal [ULN] of aspartate aminotransferase (AST) also known as SGOT) were observed in about 2% of approximately 5700 patients at some time during diclofenac treatment (ALT [alanine aminotransferase] was not measured in all studies).
In a large, open-label, controlled trial of 3700 patients treated with oral diclofenac sodium for 2 to 6 months, patients were monitored first at 8 weeks and 1200 patients were monitored again at 24 weeks. Meaningful elevations of ALT and/or AST occurred in about 4% of patients and included marked elevations (greater than 8 times the ULN) in about 1% of the 3700 patients. In that open-label study, a higher incidence of borderline (less than 3 times the ULN), moderate (3 to 8 times the ULN), and marked (greater than 8 times the ULN) elevations of ALT or AST was observed in patients receiving diclofenac when compared to other NSAIDs. Elevations in transaminases were seen more frequently in patients with osteoarthritis than in those with rheumatoid arthritis.
Almost all meaningful elevations in transaminases were detected before patients became symptomatic. Abnormal tests occurred during the first 2 months of therapy with diclofenac in 42 of the 51 patients in all trials who developed marked transaminase elevations.
In postmarketing reports, cases of drug-induced hepatotoxicity have been reported in the first month, and in some cases, the first 2 months of therapy, but can occur at any time during treatment with diclofenac. Postmarketing surveillance has reported cases of severe hepatic reactions, including liver necrosis, jaundice, fulminant hepatitis with and without jaundice, and liver failure. Some of these reported cases resulted in fatalities or liver transplantation.
In a European retrospective population-based, case-controlled study, 10 cases of diclofenac associated drug-induced liver injury with current use compared with non-use of diclofenac were associated with a statistically significant 4-fold adjusted odds ratio of liver injury. In this particular study, based on an overall number of 10 cases of liver injury associated with diclofenac, the adjusted odds ratio increased further with female gender, doses of 150 mg or more, and duration of use for more than 90 days.
Physicians should measure transaminases at baseline and periodically in patients receiving long-term therapy with diclofenac, because severe hepatotoxicity may develop without a prodrome of distinguishing symptoms. The optimum times for making the first and subsequent transaminase measurements are not known. Based on clinical trial data and postmarketing experiences, transaminases should be monitored within 4 to 8 weeks after initiating treatment with diclofenac. However, severe hepatic reactions can occur at any time during treatment with diclofenac.
If abnormal liver tests persist or worsen, if clinical signs and/or symptoms consistent with liver disease develop, or if systemic manifestations occur (e.g., eosinophilia, rash, abdominal pain, diarrhea, dark urine, etc.), diclofenac sodium extended-release tablets should be discontinued immediately.
Inform patients of the warning signs and symptoms of hepatotoxicity (e.g., nausea, fatigue, lethargy, diarrhea, pruritus, jaundice, right upper quadrant tenderness, and "flu-like" symptoms). If clinical signs and symptoms consistent with liver disease develop, or if systemic manifestations occur (e.g., eosinophilia, rash, etc.), discontinue diclofenac sodium extended-release tablets immediately, and perform a clinical evaluation of the patient.
To minimize the potential risk for an adverse liver related event in patients treated with diclofenac sodium extended-release tablets, use the lowest effective dose for the shortest duration possible. Exercise caution when prescribing diclofenac sodium extended-release tablets with concomitant drugs that are known to be potentially hepatotoxic (e.g., acetaminophen, antibiotics, anti-epileptics).
Hypertension
NSAIDs, including diclofenac sodium extended-release tablets, can lead to new onset of hypertension or worsening of preexisting hypertension, either of which may contribute to the increased incidence of CV events. Patients taking angiotensin converting enzyme (ACE) inhibitors, thiazides diuretics, or loop diuretics may have impaired response to these therapies when taking NSAIDs (see PRECAUTIONS; Drug Interactions).
Monitor blood pressure (BP) during the initiation of NSAID treatment and throughout the course of therapy.
Heart Failure and Edema
The Coxib and traditional NSAID Trialists’ Collaboration meta-analysis of randomized controlled trials demonstrated an approximately 2-fold increase in hospitalization for heart failure in COX-2 selective-treated patients and nonselective NSAID-treated patients compared to placebo-treated patients. In a Danish National Registry study of patients with heart failure, NSAID use increased the risk of MI, hospitalization for heart failure, and death.
Additionally, fluid retention and edema have been observed in some patients treated with NSAIDs. Use of diclofenac may blunt the CV effects of several therapeutic agents used to treat these medical conditions (e.g., diuretics, ACE inhibitors, or angiotensin receptor blockers [ARBs]) (see PRECAUTIONS; Drug Interactions).
Avoid the use of diclofenac sodium extended-release tablets in patients with severe heart failure unless the benefits are expected to outweigh the risk of worsening heart failure. If diclofenac sodium extended-release tablets are used in patients with severe heart failure, monitor patients for signs of worsening heart failure.

Renal Toxicity and Hyperkalemia

Renal Toxicity
Long-term administration of NSAIDs has resulted in renal papillary necrosis and other renal injury.
Renal toxicity has also been seen in patients in whom renal prostaglandins have a compensatory role in the maintenance of renal perfusion. In these patients, administration of an NSAID may cause a dose-dependent reduction in prostaglandin formation and, secondarily, in renal blood flow, which may precipitate overt renal decompensation. Patients at greatest risk of this reaction are those with impaired renal function, dehydration, hypovolemia, heart failure, liver dysfunction, those taking diuretics and ACE inhibitors or ARBs, and the elderly.
Discontinuation of NSAID therapy is usually followed by recovery to the pretreatment state.
No information is available from controlled clinical studies regarding the use of diclofenac sodium extended-release tablets in patients with advanced renal disease. The renal effects of diclofenac sodium extended-release tablets may hasten the progression of renal dysfunction in patients with preexisting renal disease.
Correct volume status in dehydrated or hypovolemic patients prior to initiating diclofenac sodium extended-release tablets. Monitor renal function in patients with renal or hepatic impairment, heart failure, dehydration, or hypovolemia during use of diclofenac sodium extended-release tablets (see PRECAUTIONS; Drug Interactions). Avoid the use of diclofenac sodium extended-release tablets in patients with advanced renal disease unless the benefits are expected to outweigh the risk of worsening renal function. If diclofenac sodium extended-release tablets
are used in patients with advanced renal disease, monitor patients for signs of worsening renal function.
Hyperkalemia
Increases in serum potassium concentration, including hyperkalemia, have been reported with use of NSAIDs, even in some patients without renal impairment. In patients with normal renal function, these effects have been attributed to a hyporeninemic-hypoaldosteronism state.
Anaphylactic Reactions
Diclofenac has been associated with anaphylactic reactions in patients with and without known hypersensitivity to diclofenac and in patients with aspirin-sensitive asthma (see CONTRAINDICATIONS, WARNINGS; Exacerbation of Asthma Related to Aspirin Sensitivity).
Exacerbation of Asthma Related to Aspirin Sensitivity
A subpopulation of patients with asthma may have aspirin-sensitive asthma, which may include chronic rhinosinusitis complicated by nasal polyps; severe, potentially fatal bronchospasm; and/or intolerance to aspirin and other NSAIDs. Because cross-reactivity between aspirin and other NSAIDs has been reported in such aspirin-sensitive patients, diclofenac sodium extended-release tablets are contraindicated in patients with this form of aspirin sensitivity (see CONTRAINDICATIONS). When diclofenac sodium extended-release tablets are used in patients with preexisting asthma (without known aspirin sensitivity), monitor patients for changes in the signs and symptoms of asthma.

Serious Skin Reactions
NSAIDs, including diclofenac, can cause serious skin adverse reactions, such as exfoliative dermatitis, Stevens-Johnson Syndrome (SJS), and toxic epidermal necrolysis (TEN), which can be fatal. NSAIDs can also cause fixed drug eruption (FDE). FDE may present as a more severe variant known as generalized bullous fixed drug eruption (GBFDE), which can be life-threatening. These serious events may occur without warning. Inform patients about the signs and symptoms of serious skin reactions and to discontinue the use of diclofenac sodium extended-release tablets at the first appearance of skin rash or any other sign of hypersensitivity. Diclofenac sodium extended-release tablets are contraindicated in patients with previous serious skin reactions to NSAIDs (see CONTRAINDICATIONS).
Drug Reaction with Eosinophilia and Systemic Symptoms (DRESS)
Drug Reaction with Eosinophilia and Systemic Symptoms (DRESS) has been reported in patients taking NSAIDs, such as diclofenac sodium extended-release tablets. Some of these events have been fatal or life-threatening. DRESS typically, although not exclusively, presents with fever, rash, lymphadenopathy, and/or facial swelling. Other clinical manifestations may include hepatitis, nephritis, hematological abnormalities, myocarditis, or myositis. Sometimes symptoms of DRESS may resemble an acute viral infection. Eosinophilia is often present. Because this disorder is variable in its presentation, other organ systems not noted here may be involved. It is important to note that early manifestations of hypersensitivity, such as fever or lymphadenopathy, may be present even though rash is not evident. If such signs or symptoms are present, discontinue diclofenac sodium extended-release tablets and evaluate the patient immediately.
Fetal Toxicity
Premature Closure of Fetal Ductus Arteriosus:
Avoid use of NSAIDs, including diclofenac sodium extended-release tablets, in pregnant women at about 30 weeks gestation and later. NSAIDs, including diclofenac sodium extended-release tablets, increase the risk of premature closure of the fetal ductus arteriosus at approximately this gestational age.
Oligohydramnios/Neonatal Renal Impairment:
Use of NSAIDs, including diclofenac sodium extended-release tablets, at about 20 weeks gestation or later in pregnancy may cause fetal renal dysfunction leading to oligohydramnios and, in some cases, neonatal renal impairment. These adverse outcomes are seen, on average, after days to weeks of treatment, although oligohydramnios has been infrequently reported as soon as 48 hours after NSAID initiation.
Oligohydramnios is often, but not always, reversible with treatment discontinuation. Complications of prolonged oligohydramnios may, for example, include limb contractures and delayed lung maturation. In some postmarketing cases of impaired neonatal renal function, invasive procedures, such as exchange transfusion or dialysis were required.
If NSAID treatment is necessary between about 20 weeks and 30 weeks gestation, limit diclofenac sodium extended-release tablets use to the lowest effective dose and shortest duration possible. Consider ultrasound monitoring of amniotic fluid if diclofenac sodium extended-release tablets treatment extends beyond 48 hours. Discontinue diclofenac sodium extended-release tablets if oligohydramnios occurs and follow up according to clinical practice (see PRECAUTIONS; Pregnancy).
Hematologic Toxicity
Anemia has occurred in NSAID-treated patients. This may be due to occult or gross blood loss, fluid retention, or an incompletely described effect on erythropoiesis. If a patient treated with diclofenac sodium extended-release tablets has any signs or symptoms of anemia, monitor hemoglobin or hematocrit.
NSAIDs, including diclofenac sodium extended-release tablets, may increase the risk of bleeding events. Comorbid conditions, such as coagulation disorders, concomitant use of warfarin, other anticoagulants, antiplatelet agents (e.g., aspirin), serotonin reuptake inhibitors (SSRIs) and serotonin norepinephrine reuptake inhibitors (SNRIs) may increase this risk. Monitor these patients for signs of bleeding (see PRECAUTIONS; Drug Interactions).

PRECAUTIONS

General

Diclofenac sodium extended-release tablets, USP cannot be expected to substitute for corticosteroids or to treat corticosteroid insufficiency. Abrupt discontinuation of corticosteroids may lead to disease exacerbation. Patients on prolonged corticosteroid therapy should have their therapy tapered slowly if a decision is made to discontinue corticosteroids and the patient should be observed closely for any evidence of adverse effects, including adrenal insufficiency and exacerbation of symptoms of arthritis.
The pharmacological activity of diclofenac sodium extended-release tablets in reducing fever and inflammation may diminish the utility of these diagnostic signs in detecting complications of presumed noninfectious, painful conditions.

Information for Patients

Advise the patient to read the FDA-approved patient labeling (Medication Guide) that accompanies each prescription dispensed. Inform patients, families, or their caregivers of the following information before initiating therapy with diclofenac sodium extended-release tablets and periodically during the course of ongoing therapy.
Cardiovascular Thrombotic Events:
Advise patients to be alert for the symptoms of cardiovascular thrombotic events, including chest pain, shortness of breath, weakness, or slurring of speech, and to report any of these symptoms to their healthcare provider immediately (see WARNINGS; Cardiovascular Thrombotic Events).
Gastrointestinal Bleeding, Ulceration, and Perforation
Advise patients to report symptoms of ulcerations and bleeding, including epigastric pain, dyspepsia, melena, and hematemesis to their health care provider. In the setting of concomitant use of low-dose aspirin for cardiac prophylaxis, inform patients of the increased risk for the signs and symptoms of GI bleeding (see WARNINGS; Gastrointestinal Bleeding, Ulceration, and Perforation).
Hepatotoxicity
Inform patients of the warning signs and symptoms of hepatotoxicity (e.g., nausea, fatigue, lethargy, pruritus, jaundice, right upper quadrant tenderness, and “flu-like” symptoms). If these occur, instruct patients to stop Diclofenac sodium extended-release tablets and seek immediate medical therapy (see WARNINGS; Hepatotoxicity).
Heart Failure and Edema:
Advise patients to be alert for the symptoms of congestive heart failure, including shortness of breath, unexplained weight gain, or edema and to contact their healthcare provider if such symptoms occur (see WARNINGS; Heart Failure and Edema).
Anaphylactic Reactions
Inform patients of the signs of an anaphylactic reaction (e.g., difficulty breathing, swelling of the face or throat). Instruct patients to seek immediate emergency help if these occur (see WARNINGS; Anaphylactic Reactions).
Serious Skin Reactions, including DRESS
Advise patients to stop taking diclofenac sodium extended-release tablets immediately if they develop any type of rash or fever and contact their healthcare provider as soon as possible (see WARNINGS; Serious Skin Reactions).
Female Fertility
Advise females of reproductive potential who desire pregnancy that NSAIDs, including diclofenac sodium extended-release tablets, may be associated with a reversible delay in ovulation (see PRECAUTIONS; Carcinogenesis, Mutagenesis, Impairment of Fertility).
Fetal Toxicity
Inform pregnant women to avoid use of diclofenac sodium extended-release tablets and other NSAIDs, starting at 30 weeks' gestation because of the risk of the premature closure of the fetal ductus arteriosus. If treatment with diclofenac sodium extended-release tablets is needed for a pregnant woman between about 20 to 30 weeks gestation, advise her that she may need to be monitored for oligohydramnios, if treatment continues for longer than 48 hours. (see WARNINGS; Fetal Toxicity, PRECAUTIONS; Pregnancy).
Avoid Concomitant Use of NSAIDs
Inform patients that the concomitant use of diclofenac sodium extended-release tablets with other NSAIDs or salicylates (e.g., diflunisal, salsalate) is not recommended due to the increased risk of gastrointestinal toxicity, and little or no increase in efficacy (see WARNINGS: Gastrointestinal Bleeding, Ulceration, and Perforation and Drug Interactions). Alert patients that NSAIDs may be present in “over the counter” medications for treatment of colds, fever, or insomnia.
Use of NSAIDS and Low-Dose Aspirin
Inform patients not to use low-dose aspirin concomitantly with diclofenac sodium extended-release tablets until they talk to their healthcare provider (see PRECAUTIONS; Drug Interactions).

Masking of Inflammation and Fever

The pharmacological activity of diclofenac sodium extended-release tablets in reducing inflammation, and possibly fever, may diminish the utility of diagnostic signs in detecting infections.

Laboratory Monitoring

Because serious GI bleeding, hepatotoxicity, and renal injury can occur without warning symptoms or signs, consider monitoring patients on long-term NSAID treatment with a CBC and a chemistry profile periodically (see WARNINGS; Gastrointestinal Bleeding, Ulceration and Perforation, and Hepatotoxicity).

Drug Interactions

See Table 2 for clinically significant drug interactions with diclofenac.

Table 2. Clinically Significant Drug Interactions with Diclofenac

Drugs That Interfere with Hemostasis
Clinical Impact: | - Diclofenac and anticoagulants such as warfarin have a synergistic effect on bleeding. The concomitant use of diclofenac and anticoagulants have an increased risk of serious bleeding compared to the use of either drug alone. - Serotonin release by platelets plays an important role in hemostasis. Case-control and cohort epidemiological studies showed that concomitant use of drugs that interfere with serotonin reuptake and an NSAID may potentiate the risk of bleeding more than an NSAID alone.
Intervention: | Monitor patients with concomitant use of diclofenac sodium extended-release tablets with anticoagulants (e.g., warfarin), antiplatelet agents (e.g., aspirin), selective serotonin reuptake inhibitors (SSRIs), and serotonin norepinephrine reuptake inhibitors (SNRIs) for signs of bleeding (see WARNINGS; Hematological Toxicity).
Aspirin
Clinical Impact: | Controlled clinical studies showed that the concomitant use of NSAIDs and analgesic doses of aspirin does not produce any greater therapeutic effect than the use of NSAIDs alone. In a clinical study, the concomitant use of an NSAID and aspirin was associated with a significantly increased incidence of GI adverse reactions as compared to use of the NSAID alone (see Warnings; Gastrointestinal Bleeding, Ulceration, and Perforation).
Intervention: | Concomitant use of diclofenac sodium extended-release tablets and analgesic doses of aspirin is not generally recommended because of the increased risk of bleeding (see WARNINGS; Hematological Toxicity). Diclofenac sodium extended-release tablets are not a substitute for low dose aspirin for cardiovascular protection.
ACE Inhibitors, Angiotensin Receptor Blockers, and Beta- Blockers
Clinical Impact: | • NSAIDs may diminish the antihypertensive effect of angiotensin converting enzyme (ACE) inhibitors, angiotensin receptor blockers (ARBs), or beta-blockers (including propranolol). • In patients who are elderly, volume-depleted (including those on diuretic therapy), or have renal impairment, coadministration of an NSAID with ACE inhibitors or ARBs may result in deterioration of renal function, including possible acute renal failure. These effects are usually reversible.
Intervention: | • During concomitant use of diclofenac sodium extended-release tablets and ACE-inhibitors, ARBs, or beta-blockers, monitor blood pressure to ensure that the desired blood pressure is obtained. • During concomitant use of diclofenac sodium extended-release tablets and ACE-inhibitors or ARBs in patients who are elderly, volume-depleted, or have impaired renal function, monitor for signs of worsening renal function (see WARNINGS; Renal Toxicity and Hyperkalemia). • When these drugs are administered concomitantly, patients should be adequately hydrated. Assess renal function at the beginning of the concomitant treatment and periodically thereafter.
Diuretics
Clinical Impact: | Clinical studies, as well as post-marketing observations, showed that NSAIDs reduced the natriuretic effect of loop diuretics (e.g., furosemide) and thiazide diuretics in some patients. This effect has been attributed to the NSAIDinhibition of renal prostaglandin synthesis.
Intervention: | During concomitant use of diclofenac sodium extended-release tablets with diuretics, observe patients for signs of worsening renal function, in addition to assuring diuretic efficacy, including antihypertensive effects (see WARNINGS; Renal Toxicity and Hyperkalemia).
Digoxin
Clinical Impact: | The concomitant use of diclofenac with digoxin has been reported to increase the serum concentration and prolong the half-life of digoxin.
Intervention: | During concomitant use of diclofenac sodium extended-release tablets and digoxin, monitor serum digoxin levels.
Lithium
Clinical Impact: | NSAIDs have produced elevations in plasma lithium levels and reductions in renal lithium clearance. The mean minimum lithium concentration increased 15%, and the renal clearance decreased by approximately 20%. This effect has been attributed to NSAID inhibition of renal prostaglandin synthesis.
Intervention: | During concomitant use of diclofenac sodium extended-release tablets and lithium, monitor patients for signs of lithium toxicity.
Methotrexate
Clinical Impact: | Concomitant use of NSAIDs and methotrexate may increase the risk for methotrexate toxicity (e.g., neutropenia, thrombocytopenia, renal dysfunction).
Intervention: | During concomitant use of diclofenac sodium extended-release tablets and methotrexate, monitor patients for methotrexate toxicity.
Cyclosporine
Clinical Impact: | Concomitant use of diclofenac sodium extended-release tablets and cyclosporine may increase cyclosporine’s nephrotoxicity.
Intervention: | During concomitant use of diclofenac sodium extended-release tablets and cyclosporine, monitor patients for signs of worsening renal function.
NSAIDs and Salicylates
Clinical Impact: | Concomitant use of diclofenac with other NSAIDs or salicylates (e.g., diflunisal, salsalate) increases the risk of GI toxicity, with little or no increase in efficacy (see WARNINGS; Gastrointestinal Bleeding, Ulceration, and Perforation).
Intervention: | The concomitant use of diclofenac with other NSAIDs or salicylates is not recommended.
Pemetrexed
Clinical Impact: | Concomitant use of diclofenac sodium extended-release tablets and pemetrexed may increase the risk of pemetrexed-associated myelosuppression, renal, and GI toxicity (see the pemetrexed prescribing information).
Intervention: | During concomitant use of diclofenac sodium extended-release tablets and pemetrexed, in patients with renal impairment whose creatinine clearance ranges from 45 to 79 mL/min, monitor for myelosuppression, renal and GI toxicity. NSAIDs with short elimination half-lives (e.g., diclofenac, indomethacin) should be avoided for a period of 2 days before, the day of, and 2 days following administration of pemetrexed. In the absence of data regarding potential interaction between pemetrexed and NSAIDs with longer half-lives (e.g., meloxicam, nabumetone), patients taking these NSAIDs should interrupt dosing for at least 5 days before, the day of, and 2 days following pemetrexed administration.
CYP2C9 Inhibitors or Inducers:
Clinical Impact: | Diclofenac is metabolized by cytochrome P450 enzymes, predominantly by CYP2C9. Coadministration of diclofenac with CYP2C9 inhibitors (e.g., voriconazole) may enhance the exposure and toxicity of diclofenac whereas coadministration with CYP2C9 inducers (e.g., rifampin) may lead to compromised efficacy of diclofenac.
Intervention: | A dosage adjustment may be warranted when diclofenac is administered with CYP2C9 inhibitors or inducers (see CLINICAL PHARMACOLOGY; Pharmacokinetics).

Carcinogenesis, Mutagenesis, Impairment of Fertility

Carcinogenesis
Long-term carcinogenicity studies in rats given diclofenac sodium up to 2 mg/kg/day (approximately 0.1 times the maximum recommended human dose (MRHD) of diclofenac sodium extended-release tablets, 200 mg/day, based on body surface area (BSA) comparison) have revealed no significant increase in tumor incidence. A 2-year carcinogenicity study conducted in mice employing diclofenac sodium at doses up to 0.3 mg/kg/day (approximately 0.007 times the MRHD based on BSA comparison) in males and 1 mg/kg/day (approximately 0.02 times the MRHD based on BSA comparison) in females did not reveal any oncogenic potential.
Mutagenesis
Diclofenac sodium did not show mutagenic activity in in vitro point mutation assays in mammalian (mouse lymphoma) and microbial (yeast, Ames) test systems and was nonmutagenic in several mammalian in vitro and in vivo tests, including dominant lethal and male germinal epithelial chromosomal studies in mice, and nucleus anomaly and chromosomal aberration studies in Chinese hamsters.
Impairment of Fertility
Diclofenac sodium administered to male and female rats at 4 mg/kg/day (approximately 0.2 times the MRHD based on BSA comparison) did not affect fertility.
Based on the mechanism of action, the use of prostaglandin-mediated NSAIDs, including diclofenac sodium extended-release tablets, may delay or prevent rupture of ovarian follicles, which has been associated with reversible infertility in some women. Published animal studies have shown that administration of prostaglandin synthesis inhibitors has the potential to disrupt prostaglandin-mediated follicular rupture required for ovulation. Small studies in women treated with NSAIDs have also shown a reversible delay in ovulation. Consider withdrawal of NSAIDs, including diclofenac sodium extended-release tablets, in women who have difficulties conceiving or who are undergoing investigation of infertility.

Pregnancy

Risk Summary
Use of NSAIDs, including diclofenac sodium extended-release tablets, can cause premature closure of the fetal ductus arteriosus and fetal renal dysfunction leading to oligohydramnios and, in some cases, neonatal renal impairment. Because of these risks, limit dose and duration of diclofenac sodium extended-release tablets use between about 20 and 30 weeks of gestation, and avoid diclofenac sodium extended-release tablets use at about 30 weeks of gestation and later in pregnancy (see WARNINGS; Fetal Toxicity).
Premature Closure of Fetal Ductus Arteriosus
Use of NSAIDs, including diclofenac sodium extended-release tablets, at about 30 weeks gestation or later in pregnancy increases the risk of premature closure of the fetal ductus arteriosus.
Oligohydramnios/Neonatal Renal Impairment
Use of NSAIDs at about 20 weeks gestation or later in pregnancy has been associated with cases of fetal renal dysfunction leading to oligohydramnios, and in some cases, neonatal renal impairment.

There are no adequate and well-controlled studies of diclofenac sodium in pregnant women.
Data from observational studies regarding potential embryo-fetal risks of NSAID use in women in the first or second trimesters of pregnancy are inconclusive. In animal reproduction studies, no evidence of teratogenicity was observed in mice, rats, or rabbits given diclofenac daily during the period of organogenesis at doses up to approximately 0.5, 0.5, and 1 times, respectively, the maximum recommended human dose (MRHD) of diclofenac sodium extended-release tablets, despite the presence of maternal and fetal toxicity at these doses [see Data]. Based on published animal data, prostaglandins have been shown to have an important role in endometrial vascular permeability, blastocyst implantation, and decidualization. In animal studies, administration of prostaglandin synthesis inhibitors, such as diclofenac, resulted in increased pre- and post-implantation loss. Prostaglandins also have been shown to have an important role in fetal kidney development. In published animal studies, prostaglandin synthesis inhibitors have been reported to impair kidney development when administered at clinically relevant doses.
The estimated background risk of major birth defects and miscarriage for the indicated population(s) is unknown. All pregnancies have a background risk of birth defect, loss, or other adverse outcomes. In the U.S. general population, the estimated background risk of major birth defects and miscarriage in clinically recognized pregnancies is 2% to 4% and 15% to 20%, respectively.

Clinical Considerations

Fetal/Neonatal Adverse Reactions

Premature Closure of Fetal Ductus Arteriosus:

Avoid use of NSAIDs in women at about 30 weeks gestation and later in pregnancy, because NSAIDs, including diclofenac sodium extended-release tablets, can cause premature closure of the fetal ductus arteriosus (see WARNINGS; Fetal Toxicity).

Oligohydramnios/Neonatal Renal Impairment:

If an NSAID is necessary at about 20 weeks gestation or later in pregnancy, limit the use to the lowest effective dose and shortest duration possible. If diclofenac sodium extended-release tablets treatment extends beyond 48 hours, consider monitoring with ultrasound for oligohydramnios. If oligohydramnios occurs, discontinue diclofenac sodium extended-release tablets and follow up according to clinical practice (see WARNINGS; Fetal Toxicity).

Labor or Delivery

There are no studies on the effects of diclofenac sodium extended-release tablets during labor or delivery. In animal studies, NSAIDS, including diclofenac, inhibit prostaglandin synthesis, cause delayed parturition, and increase the incidence of stillbirth.

Data
Human Data
Premature Closure of Fetal Ductus Arteriosus:
Published literature reports that the use of NSAIDs at about 30 weeks of gestation and later in pregnancy may cause premature closure of the fetal ductus arteriosus.
Oligohydramnios/Neonatal Renal Impairment:
Published studies and postmarketing reports describe maternal NSAID use at about 20 weeks gestation or later in pregnancy associated with fetal renal dysfunction leading to oligohydramnios, and in some cases, neonatal renal impairment. These adverse outcomes are seen, on average, after days to weeks of treatment, although oligohydramnios has been infrequently reported as soon as 48 hours after NSAID initiation. In many cases, but not all, the decrease in amniotic fluid was transient and reversible with cessation of the drug. There have been a limited number of case reports of maternal NSAID use and neonatal renal dysfunction without oligohydramnios, some of which were irreversible. Some cases of neonatal renal dysfunction required treatment with invasive procedures, such as exchange transfusion or dialysis.
Methodological limitations of these post-marketing studies and reports include lack of a control group; limited information regarding dose, duration, and timing of drug exposure; and concomitant use of other medications. These limitations preclude establishing a reliable estimate of the risk of adverse fetal and neonatal outcomes with maternal NSAID use. Because the published safety data on neonatal outcomes involved mostly preterm infants, the generalizability of certain reported risks to the full-term infant exposed to NSAIDs through maternal use is uncertain.
Animal Data
Reproductive and developmental studies in animals demonstrated that diclofenac sodium administration during organogenesis did not produce teratogenicity despite the induction of maternal toxicity and fetal toxicity in mice at oral doses up to 20 mg/kg/day (approximately 0.5 times the maximum recommended human dose [MRHD] of diclofenac sodium extended-release tablets, 200 mg/day, based on body surface area (BSA) comparison), and in rats and rabbits at oral doses up to 10 mg/kg/day (approximately 0.5 and 1 times, respectively, the MRHD based on BSA comparison). In a study in which pregnant rats were orally administered 2 or 4 mg/kg diclofenac (0.1 and 0.2 times the MRHD based on BSA) from Gestation Day 15 through Lactation Day 21, significant maternal toxicity (peritonitis, mortality) was noted. These maternally toxic doses were associated with dystocia, prolonged gestation, reduced fetal weights and growth, and reduced fetal survival.
Diclofenac has been shown to cross the placental barrier in mice, rats, and humans.

Nursing Mothers

Risk Summary
Based on available data, diclofenac may be present in human milk. The developmental and health benefits of breastfeeding should be considered along with the mother’s clinical need for diclofenac sodium extended-release tablets and any potential adverse effects on the breastfed infant from the diclofenac sodium extended-release tablets or from the underlying maternal condition.
Data
One woman treated orally with a diclofenac salt, 150 mg/day, had a milk diclofenac level of 100 mcg/L, equivalent to an infant dose of about 0.03 mg/kg/day. Diclofenac was not detectable in breast milk in 12 women using diclofenac (after either 100 mg/day orally for 7 days or a single 50 mg intramuscular dose administered in the immediate postpartum period).

Pediatric Use

Safety and effectiveness in pediatric patients have not been established.

Geriatric Use

Elderly patients, compared to younger patients, are at greater risk for NSAID-associated serious cardiovascular, gastrointestinal, and/ or renal adverse reactions. If the anticipated benefit for the elderly patient outweighs these potential risks, start dosing at the low end of the dosing range, and monitor patients for adverse effects (see WARNINGS; Cardiovascular Thrombotic Events, Gastrointestinal Bleeding, Ulceration, and Perforation, Hepatotoxicity, Renal Toxicity and Hyperkalemia, PRECAUTIONS; Laboratory Monitoring).
Diclofenac is known to be substantially excreted by the kidney, and the risk of adverse reactions to this drug may be greater in patients with impaired renal function. Because elderly patients are more likely to have decreased renal function, care should be taken in dose selection, and it may be useful to monitor renal function (see CLINICAL PHARMACOLOGY, ADVERSE REACTIONS).

ADVERSE REACTIONS

The following adverse reactions are discussed in greater detail in other sections of the labeling:
• Cardiovascular Thrombotic Events (see WARNINGS)
• GI Bleeding, Ulceration and Perforation (see WARNINGS)
• Hepatotoxicity (see WARNINGS)
• Hypertension (see WARNINGS)
• Heart Failure and Edema (see WARNINGS)
• Renal Toxicity and Hyperkalemia (see WARNINGS)
• Anaphylactic Reactions (see WARNINGS)
• Serious Skin Reactions (see WARNINGS)
• Hematologic Toxicity (see WARNINGS)

Clinical Trials Experience

Because clinical trials are conducted under widely varying conditions, adverse reaction rates observed in the clinical trials of a drug cannot be directly compared to rates in the clinical trials of another drug and may not reflect the rates observed in practice.
In patients taking diclofenac sodium extended-release tablets, USP or other NSAIDs, the most frequently reported adverse experiences occurring in approximately 1% to 10% of patients are:
Gastrointestinal experiences including: abdominal pain, constipation, diarrhea, dyspepsia, flatulence, gross bleeding/perforation, heartburn, nausea, GI ulcers (gastric/duodenal) and vomiting.
Abnormal renal function, anemia, dizziness, edema, elevated liver enzymes, headaches, increased bleeding time, pruritus, rashes and tinnitus.
Additional adverse experiences reported occasionally include:
Body as a Whole: fever, infection, sepsis
Cardiovascular System: congestive heart failure, hypertension,
tachycardia, syncope
Digestive System: dry mouth, esophagitis, gastric/peptic ulcers, gastritis, gastrointestinal bleeding, glossitis, hematemesis, hepatitis,
jaundice
Hemic and Lymphatic System: ecchymosis, eosinophilia, leukopenia, melena, purpura, rectal bleeding, stomatitis, thrombocytopenia
Metabolic and Nutritional: weight changes
Nervous System: anxiety, asthenia, confusion, depression, dream abnormalities, drowsiness, insomnia, malaise, nervousness, paresthesia, somnolence, tremors, vertigo
Respiratory System: asthma, dyspnea
Skin and Appendages: alopecia, photosensitivity, sweating increased
Special Senses: blurred vision
Urogenital System: cystitis, dysuria, hematuria, interstitial nephritis, oliguria/polyuria, proteinuria, renal failure.
Other adverse reactions, which occur rarely are:
Body as a Whole: anaphylactic reactions, appetite changes, death
Cardiovascular System: arrhythmia, hypotension, myocardial infarction, palpitations, vasculitis
Digestive System: colitis, eructation, fulminant hepatitis with and without jaundice, liver failure, liver necrosis, pancreatitis
Hemic and Lymphatic System: agranulocytosis, hemolytic anemia, aplastic anemia, lymphadenopathy, pancytopenia
Metabolic and Nutritional: hyperglycemia
Nervous System: convulsions, coma, hallucinations, meningitis
Respiratory System: respiratory depression, pneumonia
Skin and Appendages: angioedema, toxic epidermal necrolysis, erythema multiforme, exfoliative dermatitis, Stevens-Johnson syndrome, fixed drug eruption (FDE), urticaria
Special Senses: conjunctivitis, hearing impairment.
To report SUSPECTED ADVERSE EVENTS, contact Edenbridge Pharmaceuticals, LLC at 877-381-3336 or FDA at 1-800-FDA-1088 or http://www.fda.gov/medwatch for voluntary reporting of adverse reactions.

OVERDOSAGE

Symptoms following acute NSAID overdosages have been typically limited to lethargy, drowsiness, nausea, vomiting, and epigastric pain, which have been generally reversible with supportive care. Gastrointestinal bleeding has occurred. Hypertension, acute renal failure, respiratory depression and coma have occurred, but were rare. (seeWARNINGS; Cardiovascular Thrombotic Events, Gastrointestinal Bleeding, Ulceration, and Perforation, Hypertension, Renal Toxicity and Hyperkalemia).
Manage patients with symptomatic and supportive care following an NSAID overdosage. There are no specific antidotes. Consider emesis and/or activated charcoal (60 to 100 grams in adults, 1 to 2 grams per kg in pediatric patients) and/or osmotic cathartic in symptomatic patients seen within four hours of ingestion or in patients with a large overdose (5 to 10 times the recommended dosage). Forced diuresis, alkalinization of urine, hemodialysis, or hemoperfusion may not be useful due to high protein binding.
For additional information about overdosage treatment contact a poison control center (1-800-222-1222).

DOSAGE AND ADMINISTRATION

Carefully consider the potential benefits and risks of diclofenac sodium extended-release tablets, USP and other treatment options before deciding to use diclofenac sodium extended release tablets. Use the lowest effective dose for the shortest duration consistent with individual patient treatment goals (see WARNINGS).
After observing the response to initial therapy with diclofenac sodium extended-release tablets, the dose and frequency should be adjusted to suit an individual patient’s needs.
For the relief of osteoarthritis, the recommended dosage is 100 mg daily.
For the relief of rheumatoid arthritis, the recommended dosage is 100 mg daily. In the rare patient where diclofenac sodium extended-release tablets 100 mg/day are unsatisfactory, the dose may be increased to 100 mg twice a day if the benefits outweigh the clinical risks of increased side effects.
Different formulations of diclofenac (diclofenac sodium enteric-coated tablets; diclofenac sodium extended-release tablets, USP, diclofenac potassium immediate-release tablets) are not necessarily bioequivalent even if the milligram strength is the same.

HOW SUPPLIED

Diclofenac sodium extended-release tablets, USP
100 mg - Pink round convex film coated tablet debossed with DX 41 on one side.
Bottle of 100 NDC 42799-953-01.
Store at 20° to 25°C (68° to 77°F) [See USP Controlled Room Temperature]. Protect from moisture.
Dispense in tight container (USP).

Manufactured for:
Edenbridge Pharmaceuticals, LLC

DBA Dexcel Pharma USA

Parsippany, NJ 07054

877-381-3336

Manufactured by:
Dexcel Pharma Technologies Ltd.,

Israel

Revised: 02/2025

Medication Guide for Nonsteroidal Anti-Inflammatory Drugs(NSAIDs)

What is the most important information I should know about medicines called Non-Steroidal Anti-Inflammatory Drugs (NSAIDs)?
NSAIDs can cause serious side effects, including:
• Increased risk of a heart attack or stroke that can lead to death.
This risk may happen early in treatment and may increase:
• with increasing doses of NSAIDs
• with longer use of NSAIDs
Do not take NSAIDs right before or after a heart surgery called a “coronary artery bypass graft (CABG).” Avoid taking NSAIDs after a recent heart attack, unless your healthcare provider tells you to.
You may have an increased risk of another heart attack if you take NSAIDs after a recent heart attack.
• Increased risk of bleeding, ulcers, and tears (perforation) of the esophagus (tube leading from the mouth to the stomach), stomach and intestines:
• any time during use
• without warning symptoms
• that may cause death
The risk of getting an ulcer or bleeding increases with:
• past history of stomach ulcers, or stomach or intestinal bleeding with use of NSAIDs
• taking medicines called “corticosteroids”, “anticoagulants”, “SSRIs”, or “SNRIs”
• increasing doses of NSAIDs
• longer use of NSAIDs
• smoking
• drinking alcohol
• older age
• poor health
• advanced liver disease
• bleeding problems

NSAIDs should only be used:

• exactly as prescribed
• at the lowest dose possible for your treatment
• for the shortest time needed
What are NSAIDs?
NSAIDs are used to treat pain and redness, swelling, and heat (inflammation) from medical conditions, such as different types of arthritis, menstrual cramps, and other types of short-term pain.
Who should not take NSAIDs?
Do not take NSAIDs:
• if you had an asthma attack, hives, or other allergic reaction with aspirin or any other NSAIDs.
• right before or after heart bypass surgery.
Before taking NSAIDs, tell your healthcare provider about all of your medical conditions, including if you:
• have liver or kidney problems
• have high blood pressure
• have asthma
• are pregnant or plan to become pregnant. Taking NSAIDs at about 20 weeks of pregnancy or later may harm your unborn baby. If you need to take NSAIDs for more than 2 days when you are between 20 and 30 weeks of pregnancy, your healthcare provider may need to monitor the amount of fluid in your womb around your baby. You should not take NSAIDs after about 30 weeks of pregnancy.
• are breastfeeding or plan to breastfeed.
Tell your healthcare provider about all of the medicines you take, including prescription or over-the-counter medicines, vitamins or herbal supplements. NSAIDs and some other medicines can interact with each other and cause serious side effects. Do not start taking any new medicine without talking to your healthcare provider first.
What are the possible side effects of NSAIDs?
NSAIDs can cause serious side effects, including:
See “What is the most important information I should know about medicines called Nonsteroidal Anti-inflammatory Drugs (NSAIDs)?
• new or worse high blood pressure
• heart failure
• liver problems including liver failure
• kidney problems including kidney failure
• low red blood cells (anemia)
• life-threatening skin reactions
• life-threatening allergic reactions
Other side effects of NSAIDs include: stomach pain, constipation, diarrhea, gas, heartburn, nausea, vomiting, and dizziness
Get emergency help right away if you have any of the following symptoms:
• shortness of breath or trouble breathing
• chest pain
• weakness in one part or side of your body
• slurred speech
• swelling of the face or throat
Stop taking your NSAID and call your healthcare provider right away if you get any of the following symptoms:
• nausea
• more tired or weaker than usual
• diarrhea
• itching
• your skin or eyes look yellow
• indigestion or stomach pain
• flu-like symptoms
• vomit blood
• there is blood in your bowel movement or it is black and sticky like tar
• unusual weight gain
• skin rash or blisters with fever
• swelling of the arms and legs, hands and feet
If you take too much of your NSAID, call your healthcare provider or get medical help right away.
These are not all the possible side effects of NSAIDs. For more information, ask your healthcare provider or pharmacist about NSAIDs. Call your doctor for medical advice about side effects. You may report side effects to FDA at 1-800-FDA-1088 or http://www.fda/gov/medwatch for voluntary reporting of adverse reactions.
Other information about NSAIDs
• Aspirin is an NSAID medicine but it does not increase the chance of a heart attack. Aspirin can cause bleeding in the brain, stomach, and intestines. Aspirin can also cause ulcers in the stomach and intestines.
• Some NSAIDs are sold in lower doses without a prescription (over-the-counter). Talk to your healthcare provider before using over-the-counter NSAIDs for more than 10 days.
General information about the safe and effective use of NSAIDs
Medicines are sometimes prescribed for purposes other than those listed in a Medication Guide. Do not use NSAIDs for a condition for which it was not prescribed. Do not give NSAIDs to other people, even if they have the same symptoms that you have. It may harm them. If you would like more information about NSAIDs, talk with your healthcare provider. You can ask your pharmacist or healthcare provider for information about NSAIDs that is written for health professionals.

Manufactured for:

Edenbridge Pharmaceuticals LLC

DBA Dexcel Pharma USA, Parsippany, NJ 07054

877-381-3336

Manufactured by:

Dexcel Pharma Technologies, Ltd., Israel

For more information, call Edenbridge Pharmaceuticals, LLC at 877-381-3336.
This Medication Guide has been approved by the U.S. Food and Drug Administration.

Revised: 02/2025